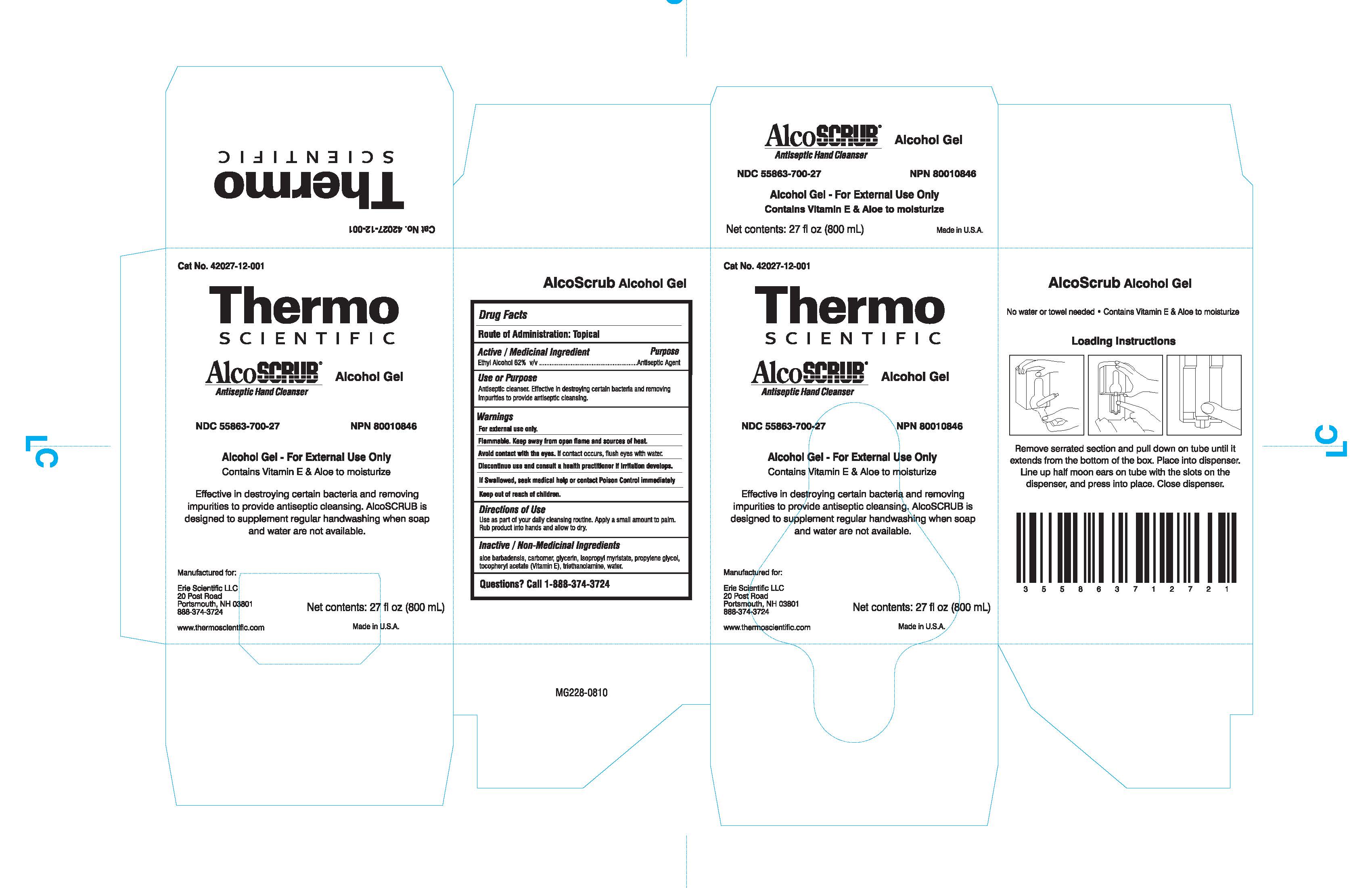 DRUG LABEL: Alcoscrub
NDC: 55863-700 | Form: LIQUID
Manufacturer: Erie Scientific, LLC.
Category: otc | Type: HUMAN OTC DRUG LABEL
Date: 20130322

ACTIVE INGREDIENTS: ALCOHOL 1 mL/1 mL
INACTIVE INGREDIENTS: Water; Glycerin; Propylene Glycol; Isopropyl Myristate; Aloe Vera Flower; .ALPHA.-TOCOPHEROL ACETATE, DL-; Trolamine

Alcoscrub

ACTIVE INGREDIENT

Ethyl Alcohol 62 % v/v

PURPOSE

For handwashing to decrease bacteria on skin.

Keep Out of Reach of Children

If swallowed, contact a physician or poison center

Indications & Usage Section

For hand cleaning to decrease bacteria on skin

WARNINGS

Flammable. Keep away from heat of flames. For external use only. Do not use in the eyes.

ASK DOCTOR

Discontinue use if redness and irritation develop. If condition persists for more than 72 hours, consult a physician. If swallowed, contact a physician or poison control center. Keep out of the reach of children.

Dosage & Administration Section

Apply a small amount to palm. Briskly rub, covering hands with product until dry.

Inactive ingredients

Water, Glycerin, Carbomer, Propylene glycol, Isopropyl Myristate, Triethanolamine, Aloe Barbadensis Leaf, Tocopheryl acetate